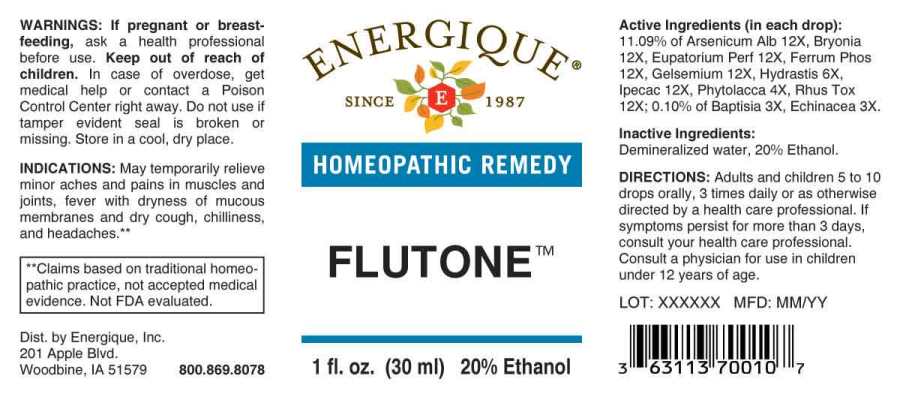 DRUG LABEL: Flutone
NDC: 44911-0514 | Form: LIQUID
Manufacturer: Energique, Inc.
Category: homeopathic | Type: HUMAN OTC DRUG LABEL
Date: 20240326

ACTIVE INGREDIENTS: BAPTISIA TINCTORIA ROOT 3 [hp_X]/1 mL; ECHINACEA ANGUSTIFOLIA WHOLE 3 [hp_X]/1 mL; PHYTOLACCA AMERICANA ROOT 4 [hp_X]/1 mL; GOLDENSEAL 6 [hp_X]/1 mL; ARSENIC TRIOXIDE 12 [hp_X]/1 mL; BRYONIA ALBA ROOT 12 [hp_X]/1 mL; EUPATORIUM PERFOLIATUM FLOWERING TOP 12 [hp_X]/1 mL; FERROSOFERRIC PHOSPHATE 12 [hp_X]/1 mL; GELSEMIUM SEMPERVIRENS ROOT 12 [hp_X]/1 mL; IPECAC 12 [hp_X]/1 mL; TOXICODENDRON PUBESCENS LEAF 12 [hp_X]/1 mL
INACTIVE INGREDIENTS: WATER; ALCOHOL

DRUG FACTS:

ACTIVE INGREDIENTS:

(in each drop): 11.09% Arsenicum Album 12X, Bryonia (Alba) 12X, Eupatorium Perfoliatum 12X, Ferrum Phosphoricum 12X, Gelsemium Sempervirens 12X, Hydrastis Canadensis 6X, Ipecacuanha 12X, Phytolacca Decandra 4X, Rhus Tox 12X; 0.10% of Baptisia Tinctoria 3X, Echinacea (Angustifolia) 3X.

INDICATIONS:

May temporarily relieve minor aches and pains in muscles and joints, fever with dryness of mucous membranes and dry cough, chilliness, and headaches.

**Claims based on traditional homeopathic practice, not accepted medical evidence. Not FDA evaluated.

WARNINGS:

If pregnant or breast-feeding, ask a health professional before use.

Keep out of reach of children. In case of overdose, get medical help or contact a Poison Control Center right away.

Do not use if tamper evident seal is broken or missing. Store in a cool, dry place.

Keep out of reach of children. In case of overdose, get medical help or contact a Poison Control Center right away.

DIRECTIONS:

Adults and children 5 to 10 drops orally, 3 times daily or as otherwise directed by a health care professional. If symptoms persist for more than 3 days, consult your health care professional. Consult a physician for use in children under 12 years of age.

INDICATIONS:

May temporarily relieve minor aches and pains in muscles and joints, fever with dryness of mucous membranes and dry cough, chilliness, and headaches.

**Claims based on traditional homeopathic practice, not accepted medical evidence. Not FDA evaluated.

INACTIVE INGREDIENTS:

Demineralized water, 20% Ethanol.

QUESTIONS:

Dist. by Energique, Inc.

201 Apple Blvd

Woodbine, IA 51579 800.869.8078

PACKAGE LABEL DISPLAY:

ENERGIQUE

SINCE 1987

HOMEOPATHIC REMEDY

FLUTONE

1 fl. oz. (30 ml)